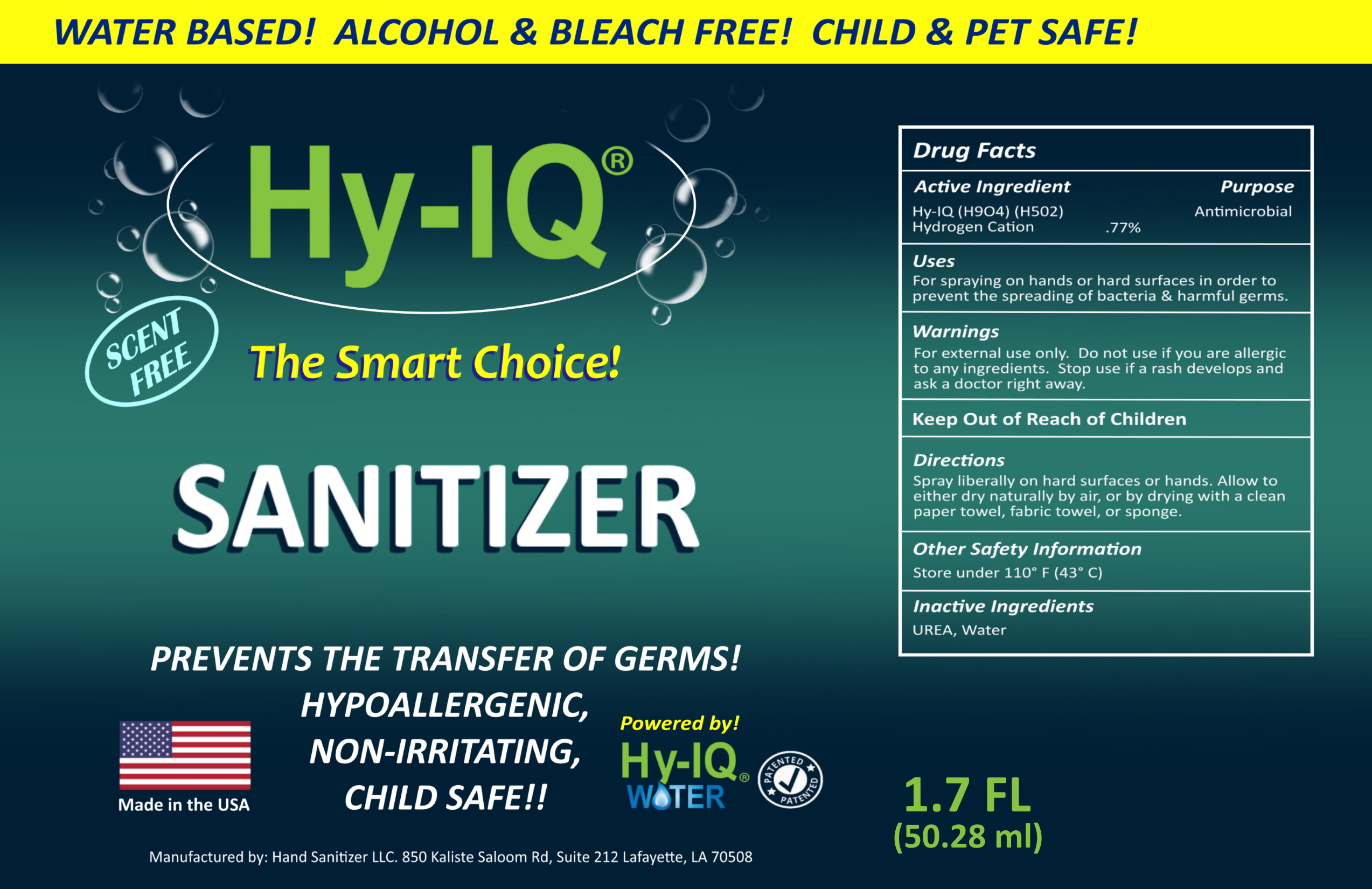 DRUG LABEL: Hi-IQ Hand Sanitizer
NDC: 76701-350 | Form: SPRAY
Manufacturer: Hand Sanitizer LLC
Category: otc | Type: HUMAN OTC DRUG LABEL
Date: 20210629

ACTIVE INGREDIENTS: HYDROGEN CATION 10 mg/1 mL
INACTIVE INGREDIENTS: WATER 940 mg/1 mL; UREA 50 mg/1 mL

ACTIVE INGREDIENT

Hy- IQ Water ([H9O4] | [H5O2])

Hydrogen Cation .77%

PURPOSE

Antimicrobial

INDICATIONS AND USAGE

For spraying on hands or hard surfaces in order to prevent the spreading of bacteria & harmful germs.

WARNINGS

For external use only. Do not use if you are allergi to any ingredients. Stop use if rash develops and ask a doctor right away.

Keep Out of Reach of Children

DOSAGE AND ADMINISTRATION

Spray liberally on hard surfaces or hands. Allow to either dry naturally by air, or by drying with a clean paper towel, fabic towel, or sponge.

OTHER SAFETY INFORMATION

Store under 110°F (43C)

INACTIVE INGREDIENT

Water, UREA